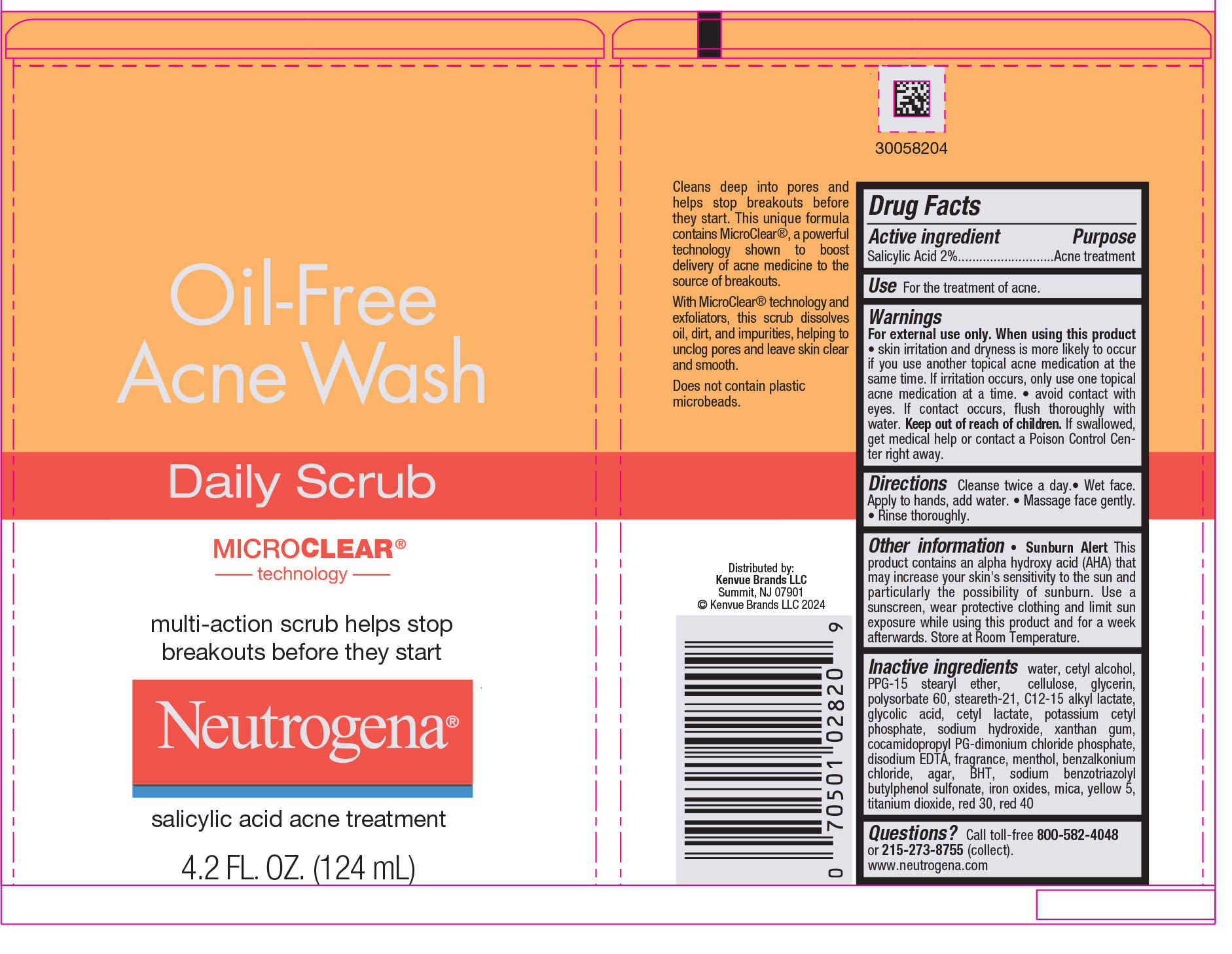 DRUG LABEL: Neutrogena Oil-Free Acne Wash Daily Scrub
NDC: 69968-0075 | Form: GEL
Manufacturer: Kenvue Brands LLC
Category: otc | Type: HUMAN OTC DRUG LABEL
Date: 20241211

ACTIVE INGREDIENTS: SALICYLIC ACID 20 mg/1 mL
INACTIVE INGREDIENTS: WATER; CETYL ALCOHOL; PPG-15 STEARYL ETHER; POWDERED CELLULOSE; STEARETH-21; GLYCERIN; POLYSORBATE 60; C12-15 ALKYL LACTATE; GLYCOLIC ACID; CETYL LACTATE; POTASSIUM CETYL PHOSPHATE; XANTHAN GUM; SODIUM HYDROXIDE; COCAMIDOPROPYL PROPYLENE GLYCOL-DIMONIUM CHLORIDE PHOSPHATE; EDETATE DISODIUM; MENTHOL, UNSPECIFIED FORM; BENZALKONIUM CHLORIDE; AGAR, UNSPECIFIED; BUTYLATED HYDROXYTOLUENE; SODIUM BENZOTRIAZOLYL BUTYLPHENOL SULFONATE; FERRIC OXIDE RED; MICA; FD&C YELLOW NO. 5; TITANIUM DIOXIDE; D&C RED NO. 30; FD&C RED NO. 40

Neutrogena® Oil-Free Acne Wash Daily Scrub

Drug Facts

Active ingredients

Salicylic Acid 2%

Purpose

Acne treatment

Use

For the treatment of acne.

Warnings

For external use only.

When using this product

- skin irritation and dryness is more likely to occur if you use another topical acne medication at the same time. If irritation occurs, only use one topical acne medication at a time.
- avoid contact with eyes. If contact occurs, flush thoroughly with water.

Keep out of reach of children.

If swallowed, get medical help or contact a Poison Control Center right away.

Directions

Cleanse twice a day.

- Wet face. Apply to hands, add water.
- Massage face gently.
- Rinse thoroughly.

Other information

- Sunburn Alert
  This product contains an alpha hydroxyl acid (AHA) that may increase your skin's sensitivity to the sun and particularly the possibility of sunburn. Use a sunscreen, wear protective clothing and limit sun exposure while using this product and for a week afterwards. Store at Room Temperature.

Inactive ingredients

water, cetyl alcohol, PPG-15 stearyl ether, cellulose, glycerin, Polysorbate 60, steareth-21, C12-15 alkyl lactate, glycolic acid, cetyl lactate, potassium cetyl phosphate, sodium hydroxide, xanthan gum, cocamedopropyl PG-dimonium chloride phosphate, disodium EDTA, fragrance, menthol, Benzalkonium chloride, agar, BHT, sodium benzotriazolyl, butylphenone sulfonate, iron oxides, mica, yellow 5, titanium dioxide, red 30, red 40

Questions?

Call toll- free 800-582-4048 or 215-273-8755 (collect).
www.neutrogena.com

Distributed by:
Kenvue Brands LLC
Summit, NJ 07901

PRINCIPAL DISPLAY PANEL - 124 mL Tube Label

Oil-Free
Acne Wash

Daily Scrub
MICRO CLEAR®
technology

multi-action scrub helps stop
breakouts before they start

Neutrogena®

salicylic acid acne treatment
4.2 FL.OZ.(124mL)